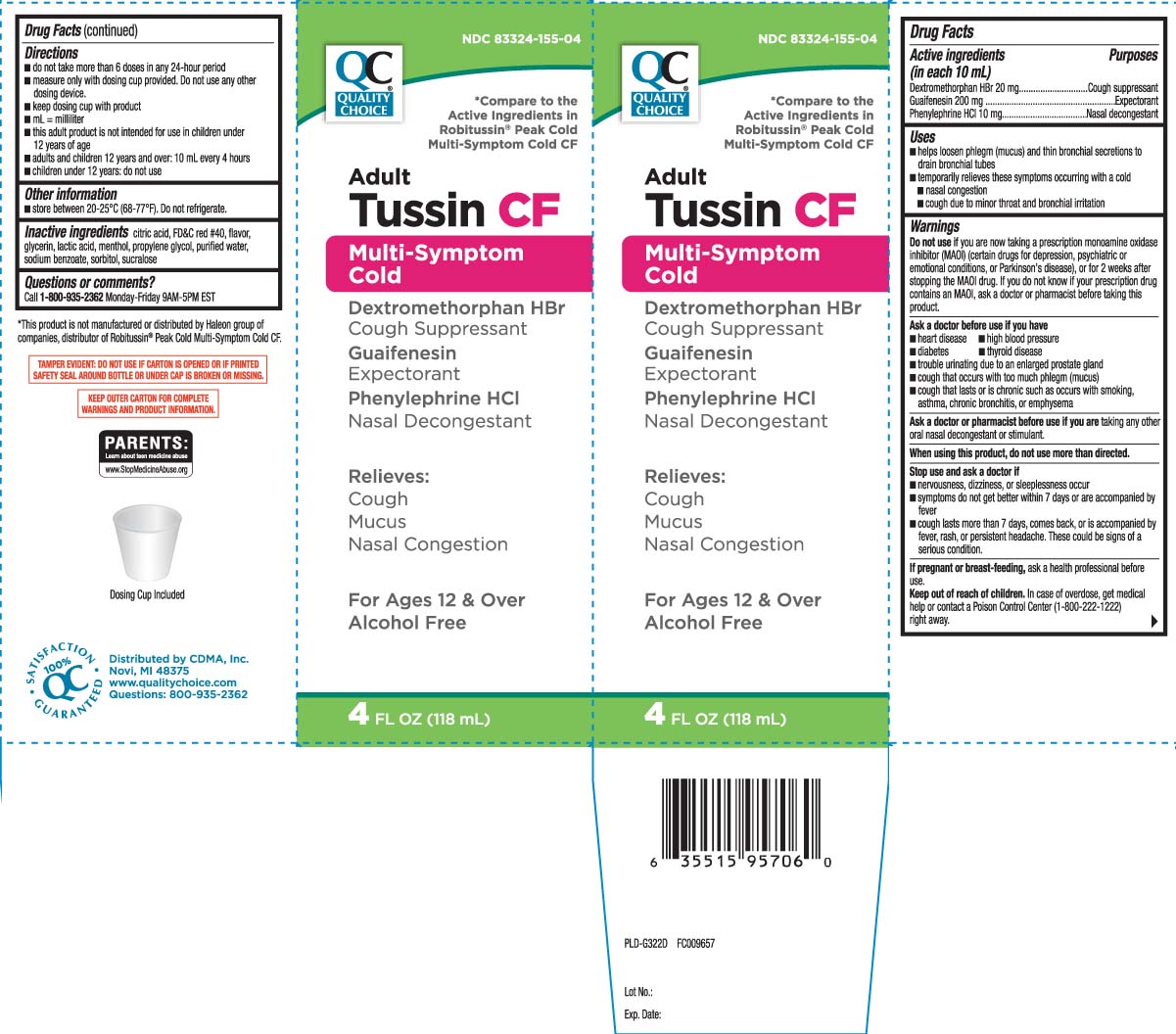 DRUG LABEL: Tussin Multi Symptom Cold CF
NDC: 83324-155 | Form: LIQUID
Manufacturer: QUALITY CHOICE (Chain Drug Marketing Association)
Category: otc | Type: HUMAN OTC DRUG LABEL
Date: 20260107

ACTIVE INGREDIENTS: DEXTROMETHORPHAN HYDROBROMIDE 20 mg/10 mL; GUAIFENESIN 200 mg/10 mL; PHENYLEPHRINE HYDROCHLORIDE 10 mg/10 mL
INACTIVE INGREDIENTS: ANHYDROUS CITRIC ACID; GLYCERIN; PROPYLENE GLYCOL; WATER; SODIUM BENZOATE; FD&C RED NO. 40; LACTIC ACID; MENTHOL; SORBITOL; SUCRALOSE

Drug Facts

Active ingredients (in each 10 mL)

Dextromethorphan HBr 20 mg

Guaifenesin 200 mg

Phenylephrine HCl 10 mg

Purposes

Cough suppressant

Expectorant

Nasal decongestant

Uses

- helps loosen phlegm (mucus) and thin bronchial secretions to drain bronchial tubes
- temporarily relieves these symptoms occurring with a cold
  - nasal congestion
  - cough due to minor throat and bronchial irritation

Warnings

Do not use

- if you are now taking a prescription monoamine oxidase inhibitor (MAOI) (certain drugs for depression, psychiatric or emotional conditions, or Parkinson’s disease), or for 2 weeks after stopping the MAOI drug. If you do not know if your prescription drug contains an MAOI, ask a doctor or pharmacist before taking this product.

Ask a doctor before use if you have

- heart disease
- high blood pressure
- diabetes
- thyroid disease
- trouble urinating due to an enlarged prostate gland
- cough that occurs with too much phlegm (mucus)
- cough that lasts or is chronic such as occurs with smoking, asthma, chronic bronchitis, or emphysema

Ask a doctor or pharmacist before use if you are

taking any other oral nasal decongestant or stimulant.

When using this product,

do not use more than directed.

Stop use and ask a doctor if

- nervousness, dizziness, or sleeplessness occur
- symptoms do not get better within 7 days or are accompanied by fever
- cough lasts more than 7 days, comes back, or is accompanied by fever, rash, or persistent headache. These could be signs of a serious condition.

If pregnant or breast-feeding,

ask a health professional before use.

Keep out of reach of children.

In case of overdose, get medical help or contact a Poison Control Center (1-800-222-1222) right away.

Directions

- do not take more than 6 doses in any 24-hour period
- measure only with dosing cup provided. Do not use any other dosing device.
- keep dosing cup with product
- mL = milliliter
- this adult product is not intended for use in children under 12 years of age
- adult and children 12 years and over: 10 mL every 4 hours
- children under 12 years: do not use

Other information

- store between 20-25°C (68°-77°F). Do not refrigerate.

Inactive ingredients

citric acid, FD&C red #40, flavor, glycerin, lactic acid, menthol, propylene glycol, purified water, sodium benzoate, sorbitol, sucralose

Questions or comments?

Call 1-800-935-2362 Monday-Friday 9AM-5PM EST

Principal display panel

*Compare to the Active Ingredients in Robitussin® Peak Cold Multi-Symptom Cold CF

Adult

Tussin CF

Multi-Symptom Cold

Dextromethorphan HBr

Cough Suppressant

Guaifenesin

Expectorant

Phenylephrine HCl

Nasal Decongestant

Relieves:

- Cough
- Mucus
- Nasal congestion

For ages 12 years & over

Alcohol Free

FL OZ (mL)

Dosing Cup Included

*This product is not manufactured or distributed by Haleon group of companies, distributor of Robitussin® Peak Cold Multi-Symptom Cold CF.

TAMPER EVIDENT: DO NOT USE IF CARTON IS OPENED OR IF PRINTED SAFETY SEAL AROUND BOTTLE OR UNDER CAP IS BROKEN OR MISSING.

KEEP OUTER CARTON FOR COMPLETE WARNINGS AND PRODUCT INFORMATION.

Distributed by CDMA, Inc.

Novi, MI 48375

www.qualitychoice.com

Questions: 800-935-2362

Package Label

Quality Choice Adult Tussin CF Multi-Symptom Cold